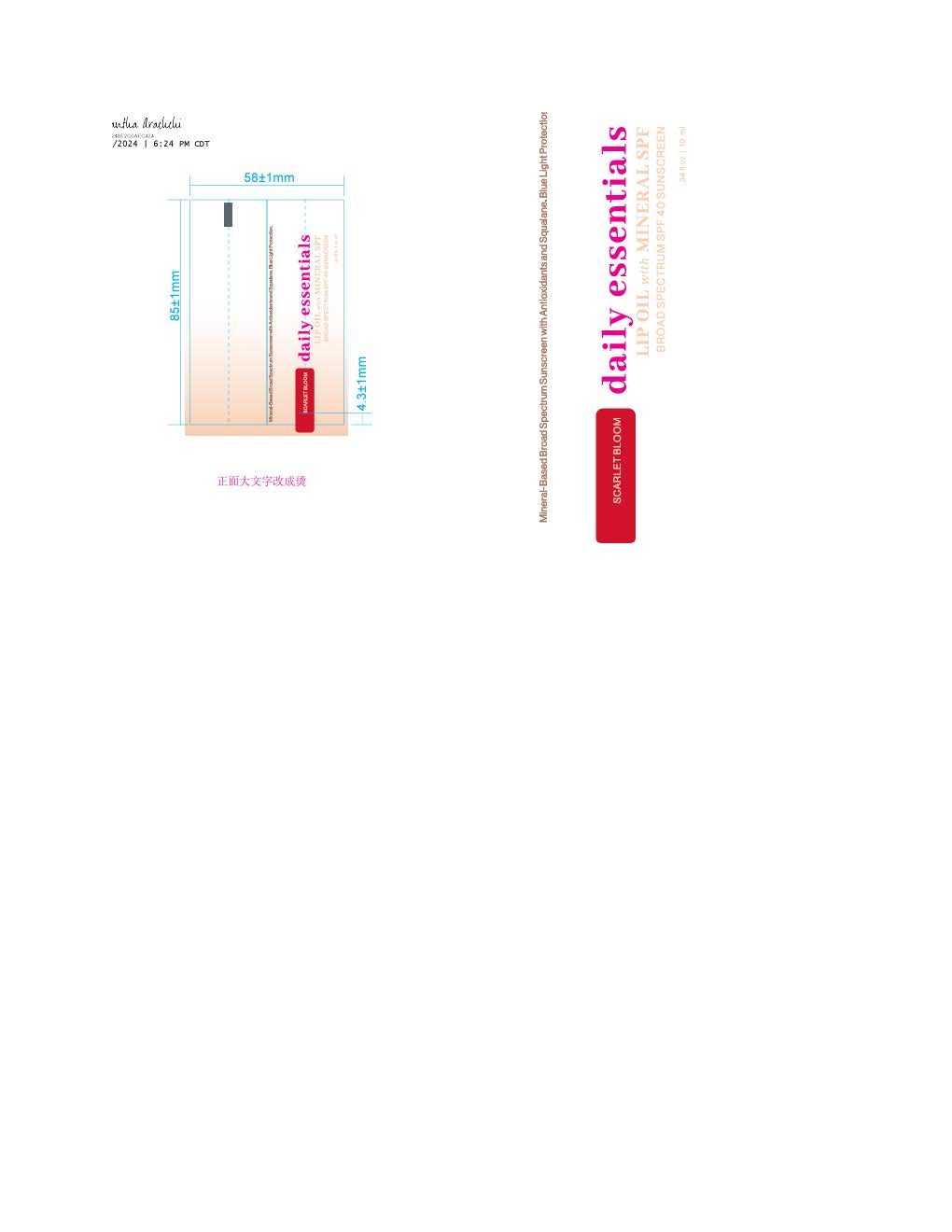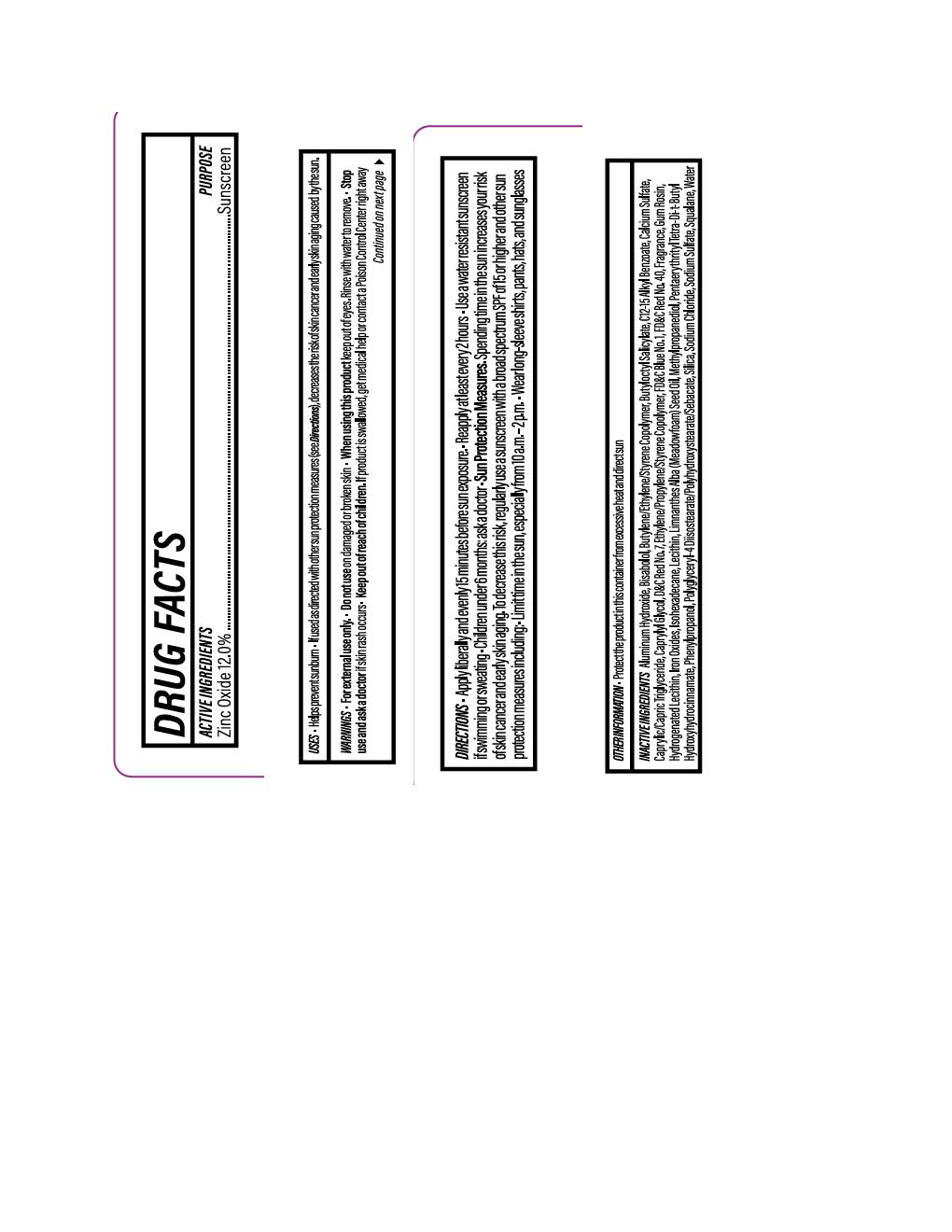 DRUG LABEL: Daily Essential Lip Oil Scarlet Bloom
NDC: 84891-1842 | Form: LOTION
Manufacturer: Solarium Brands LLC
Category: otc | Type: HUMAN OTC DRUG LABEL
Date: 20251117

ACTIVE INGREDIENTS: ZINC OXIDE 132 mg/1 mL
INACTIVE INGREDIENTS: FD&C BLUE NO. 1; CALCIUM SULFATE; SODIUM CHLORIDE; METHYLPROPANEDIOL; D&C RED NO. 7; SODIUM SULFATE; SILICON DIOXIDE; FERRIC OXIDE YELLOW; FERROSOFERRIC OXIDE; LECITHIN, SOYBEAN; SQUALANE; BUTYLOCTYL SALICYLATE; PHENYLPROPANOL; PENTAERYTHRITYL TETRA-DI-T-BUTYL HYDROXYHYDROCINNAMATE; ISOHEXADECANE; .ALPHA.-BISABOLOL, (+)-; FERRIC OXIDE RED; ALKYL (C12-15) BENZOATE; CAPRYLIC/CAPRIC TRIGLYCERIDE; CAPRYLYL GLYCOL; POLYGLYCERYL-4 DIISOSTEARATE/POLYHYDROXYSTEARATE/SEBACATE; LIMNANTHES ALBA (MEADOWFOAM) SEED OIL; WATER; ALUMINUM HYDROXIDE; FD&C RED NO. 40

Daily Essential Lip Oil Scarlet Bloom